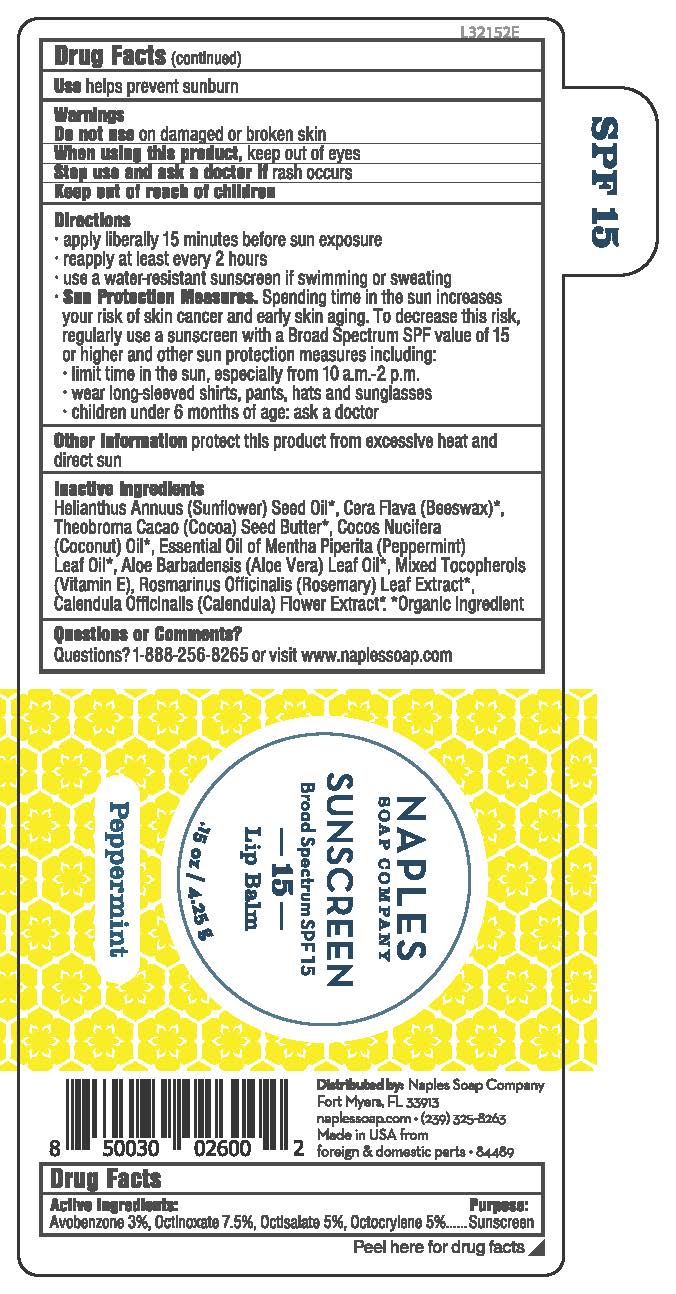 DRUG LABEL: Peppermint SPF 15 Sunscreen Lip Balm
NDC: 84489-101 | Form: STICK
Manufacturer: Naples Soap Company, Inc.
Category: otc | Type: HUMAN OTC DRUG LABEL
Date: 20260205

ACTIVE INGREDIENTS: OCTINOXATE 7.5 g/100 g; AVOBENZONE 3 g/100 g; OCTOCRYLENE 5 g/100 g; OCTISALATE 5 g/100 g
INACTIVE INGREDIENTS: PEPPERMINT; ROSEMARY; COCOA BUTTER; ALOE VERA LEAF; TOCOPHEROL; CALENDULA OFFICINALIS FLOWER; SUNFLOWER OIL; YELLOW WAX; COCONUT OIL

101S Naples Soap Co Peppermint SPF 15 Broad Spectrum Sunscreen Lip Balm

Active ingredients

Avobenzone 3%, Octinoxate 7.5%, Octisalate 5%, Octocrylene 5%

Purpose:

Sunscreen

INDICATIONS AND USAGE

Use helps prevent sunburn

Warnings

Do not use on damaged or broken skin

When using this product, keep out of eyes

Stop use and ask a doctor if rash occurs

Keep out of reach of children

Directions

- apply liberally 15 minutes before sun exposure
- reapply at least every 2 hours
- use a water resistance sunscreen if swimming or sweating
- Sun Protection Measures. Spending time in the sun increases your risk of skin cancer and early skin aging. To decrease this risk, regularly use a sunscreen with a Broad Spectrum SPF value of 15 or higher and other sun protection measures including:
- limit time in the sun, especially from 10 a.m.-2 p.m.
- wear long-sleeved shirts, pants, hats, and sunglasses
- children under 6 months of age: ask a doctor

STORAGE AND HANDLING

Other informationprotect this product from excessive heat and direct sun

Inactive ingredients

Helianthus Annuus (Sunflower) Seed Oil*, Cera Flava (Beeswax)*, Theobroma Cacao (Cocoa) Seed Butter*, Cocos Nucifera (Coconut) Oil*, Essential Oil of Mentha Piperita (Peppermint) Leaf Oil*, Aloe Barbadensis (Aloe Vera) Leaf Oil*, Mixed Tocopherols (Vitamin E), Rosmarinus Officinalis (Rosemary) Leaf Extract*, Calendula Officinalis (Calendula) Flower Extract*. *Organic Ingredient

Questions or comments?

Questions? 1-888-256-8265 or visit www.naplessoap.com

NAPLES

SOAP COMPANY

SUNSCREEN

Broad spectrum SPF 15

-15-

Lip Balm

.15 oz / 4.25 g

Peppermint

Distributed by: Naples Soap Company

Fort Myers, FL 33913

naplessoap.com - (239) 325-8263

Made in USA from

foreign & domestic parts - 84489

PACKAGE LABEL

Net Wt. 0.15 oz (4.25 g)